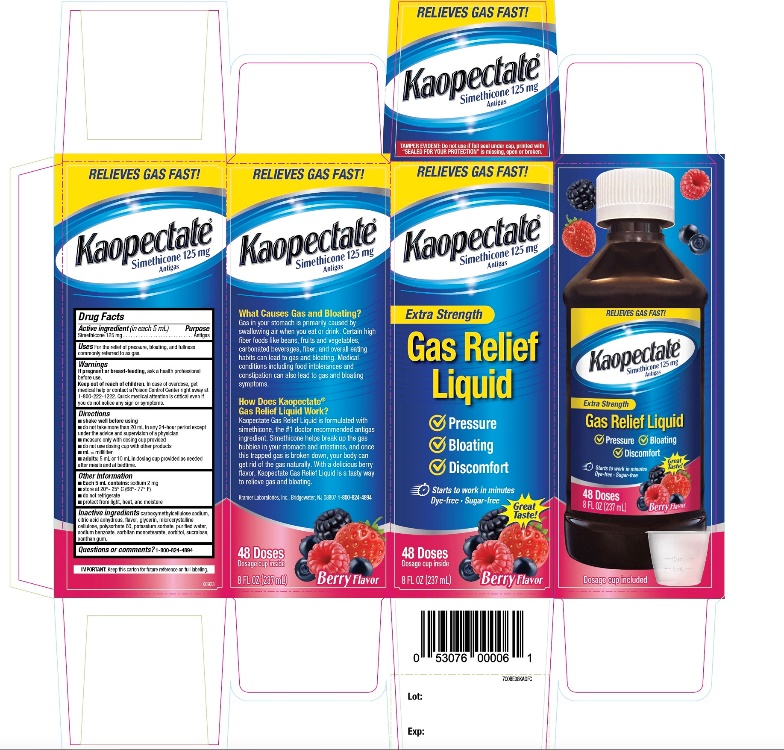 DRUG LABEL: EXTRA STRENGTH
NDC: 55505-225 | Form: LIQUID
Manufacturer: KRAMER LABORATORIES
Category: otc | Type: HUMAN OTC DRUG LABEL
Date: 20251219

ACTIVE INGREDIENTS: DIMETHICONE, UNSPECIFIED 125 mg/5 mL
INACTIVE INGREDIENTS: CARBOXYMETHYLCELLULOSE SODIUM, UNSPECIFIED; ANHYDROUS CITRIC ACID; GLYCERIN; MICROCRYSTALLINE CELLULOSE; POLYSORBATE 60; POTASSIUM SORBATE; WATER; SODIUM BENZOATE; SORBITAN MONOSTEARATE; SORBITOL; SUCRALOSE; XANTHAN GUM

KAOPECTATE Extra Strength Gas Relief Liquid

Active Ingredient (in each 5 mL)

Simethicone 125 mg

Purpose

Antigas

Uses

for the relief of pressure, bloating, and fullness commonly referred to as gas

Warnings

If pregnant or breast-feeding,

ask a health professional before use.

Keep out of reach of children.

In case of overdose, get medical help or contact a Poison Control Center right away at 1-800-222-1222. Quick medical attention is critical even if you do not notice any sign or symptoms.

Directions

- shake well before using
- do not take more than 20 mL in any 24-hour period except under the advice and supervision of a physician
- measure only with dosing cup provided
- do not use dosing cup with other products
- mL = milliliter
- adults: 5 mL or 10 mL in dosing cup provided as needed after meals and at bedtime.

Other information

- Each 5 mL contains: sodium 2 mg
- store at 20° – 25°C (68° – 77°F)
- do not refrigerate
- protect from light, heat, and moisture

Inactive ingredients

carboxymethylcellulose sodium, citric acid anhydrous, flavor, glycerin, microcrystalline cellulose, polysorbate 60, potassium sorbate, purified water, sodium benzoate, sorbitan monostearate, sorbitol, sucralose, xanthan gum.

Questions or comments?

Call 1-800-824-4894

Principal Display Panel

SAFE AND EFFECTIVE RELIEF

RELIEVES GAS FAST

NDC# 55505-225-36

Kaopectate®

Simethicone 125mg Anti-gas

Extra Strength

Gas Relief Liquid

✓ Pressure
✓ Bloating
✓ Discomfort

Starts to work in minutes

- Dye-free
- Sugar-free

Berry Flavor

48 DOSES

Dosage cup inside

8 FL OZ (237 mL)

IMPORTANT: Keep this carton for future reference on full labeling.

Distributed by

Kramer Laboratories, Inc.,

Bridgewater, NJ, 08807

1-800-824-4894

TAMPER EVIDENT: Do not use if foil seal under cap, printed with “SEALED FOR YOUR PROTECTION” is missing, open or broken.